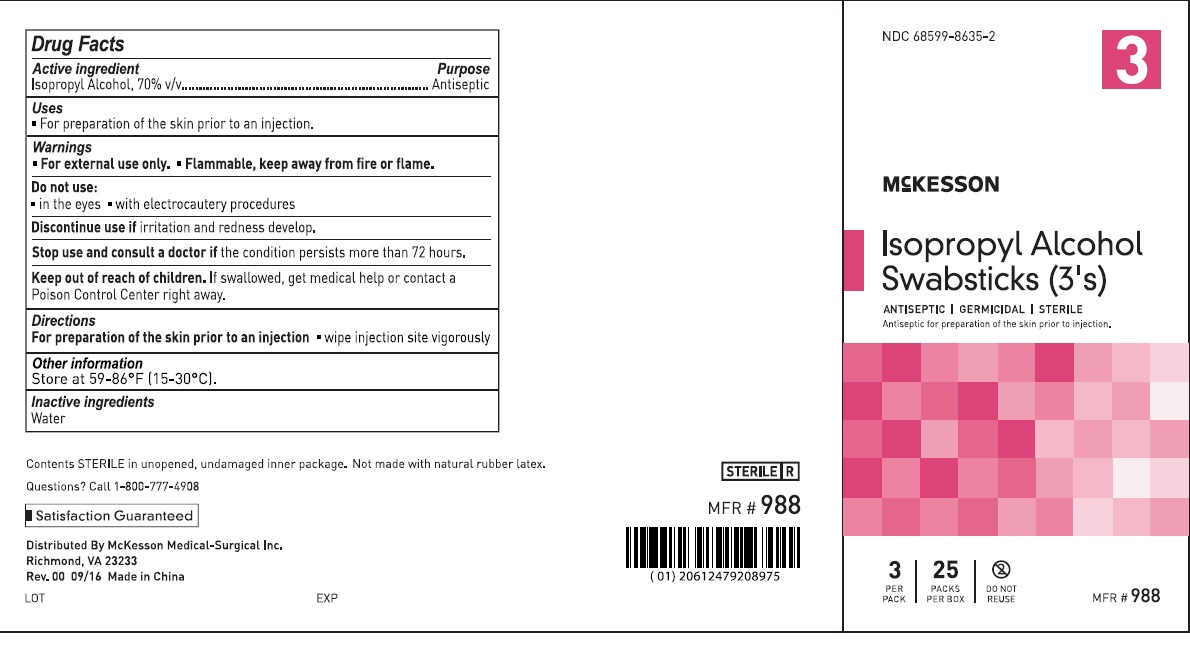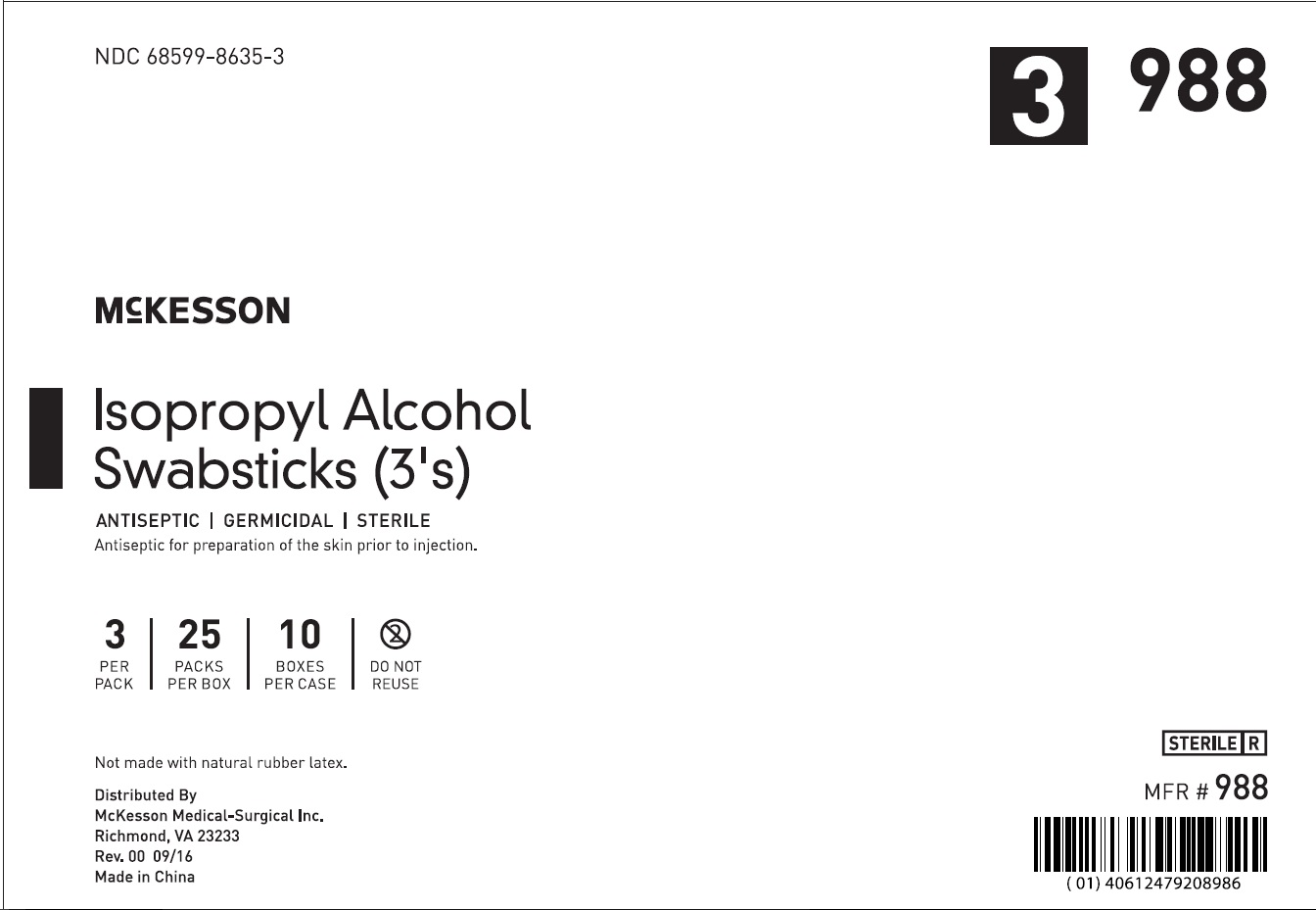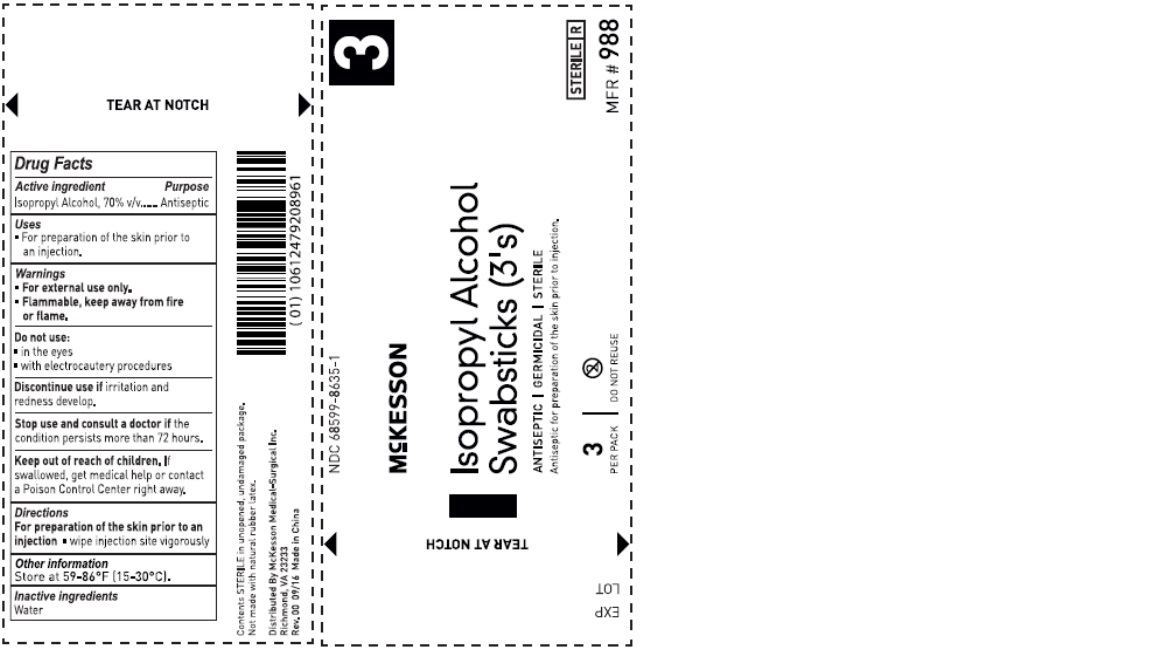 DRUG LABEL: Swabs
NDC: 68599-8635 | Form: STICK
Manufacturer: McKesson
Category: otc | Type: HUMAN OTC DRUG LABEL
Date: 20240607

ACTIVE INGREDIENTS: ISOPROPYL ALCOHOL 70 mL/100 mL
INACTIVE INGREDIENTS: WATER

ACTIVE INGREDIENT

Isopropyl Alcohol

PURPOSE

Antiseptic

INDICATIONS AND USAGE

For preparation of the skin prior to an injection

WARNINGS

For external use only. Flammable, keep away from fire or flame.

Do not use in the eyes. with electrocautery procedures

Discontinue use if irritation and redness develop.

Stop use and consult a doctor if the condition persists more than 72 hours.

KEEP OUT OF REACH OF CHILDREN

If swallowed get medical help or contact a poison control center right away.

Directions

For preparation of the skin prior to an injection. Wipe injection site vigorously.

INACTIVE INGREDIENT

Water

OTHER SAFETY INFORMATION

Store at 59º-86F (15-30ºC).